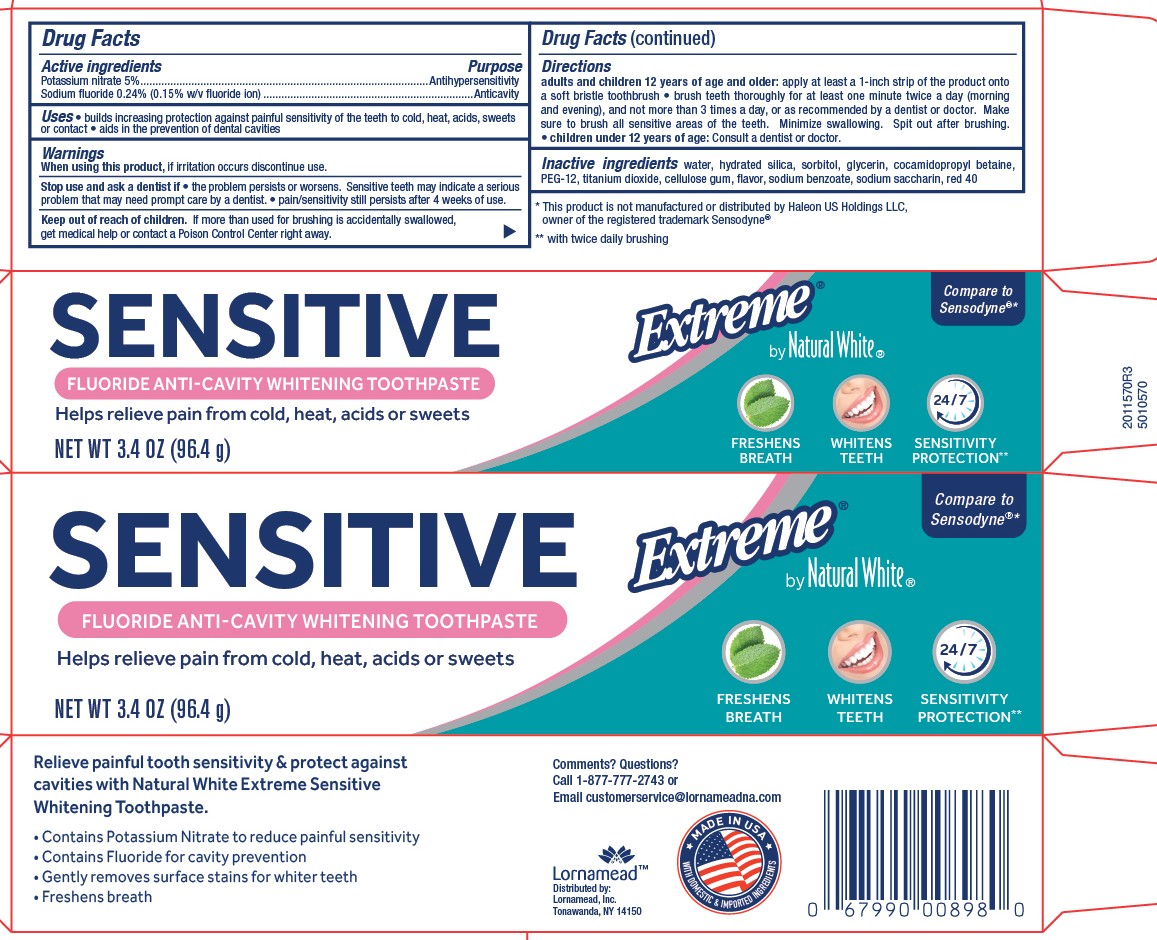 DRUG LABEL: Lornamead
NDC: 62721-0470 | Form: PASTE, DENTIFRICE
Manufacturer: Lornamead Products
Category: otc | Type: HUMAN OTC DRUG LABEL
Date: 20250808

ACTIVE INGREDIENTS: SODIUM FLUORIDE 0.15 g/100 g; POTASSIUM NITRATE 5 g/100 g
INACTIVE INGREDIENTS: WATER; SACCHARIN SODIUM; SODIUM BENZOATE; POLYETHYLENE GLYCOL 600; SODIUM TRIPOLYPHOSPHATE; TITANIUM DIOXIDE; GLYCERIN; FD&C RED NO. 40; HYDRATED SILICA; COCAMIDOPROPYL BETAINE; CARBOXYMETHYLCELLULOSE SODIUM

5010570 Natural White Extreme Sensitive Whitening

Active ingredient

Potassium nitrate 5% ................................................... Antisensitivity

Sodium fluoride 0.24% (0.15% w/v fluoride ion)............Anticavity

Uses

- builds increasing protection against painful sensitivity of the teeth to cold, heat, acids, sweets or contact
- aids in the prevention of dental cavities

When using this product, if irritation occurs discontinue use.

Keep out of reach of children. If more than used for brushing is accidentally swallowed, get medical help or contact a Poison Control Center right away.

Stop use and ask a dentist if

- the problem persists or worsens. Sensitive teeth may indicate a serious problem that may need prompt care by a dentist.
- pain/sensitivity still persists after 4 weeks of use.

Directions

Adults and children 12 years of age and older: Apply at least a 1-inch strip of the product onto a soft bristle toothbrush. Brush teeth thoroughly for at least one minute, twice a day (morning and evening) and not more than 3 times a day, or as recommneded by a dentist or doctor. Make sure to brush all sensitive areas of the teeth. Minimize swallowing. Spit out after brushing.

- children under 12 years of age: Consult a dentist or doctor.

DOSAGE AND ADMINISTRATION

Apply at least a 1-inch strip of the product onto a soft bristle toothbrush. Children under 12 years of age: ask a dentist.

Other Information

Store in a cool dry place. Keep tube capped when not in use.

Inactive ingredients

Water, Hydrated Silica, Sorbitol, Glycerin, Cocamidopropyl Betaine, PEG-12, Titanium Dioxide, Cellulose Gum, Flavor, Sodium Benzoate, Sodium Saccharin, Red 40